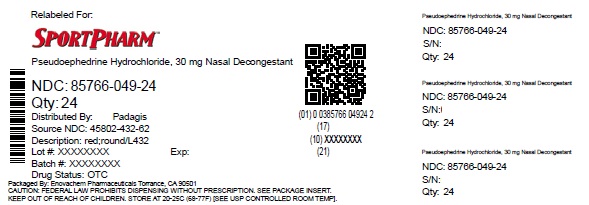 DRUG LABEL: pseudoephedrine hydrochloride
NDC: 85766-049 | Form: TABLET, FILM COATED
Manufacturer: Sportpharm LLC
Category: otc | Type: HUMAN OTC DRUG LABEL
Date: 20260206

ACTIVE INGREDIENTS: PSEUDOEPHEDRINE HYDROCHLORIDE 30 mg/1 1
INACTIVE INGREDIENTS: CARNAUBA WAX; DIBASIC CALCIUM PHOSPHATE DIHYDRATE; HYPROMELLOSE, UNSPECIFIED; MAGNESIUM STEARATE; MICROCRYSTALLINE CELLULOSE; POLYETHYLENE GLYCOL, UNSPECIFIED; POLYSORBATE 80; SILICON DIOXIDE; TITANIUM DIOXIDE; FD&C RED NO. 40 ALUMINUM LAKE

Pseudoephedrine Hydrochloride 30 mg Drug Facts

Active ingredient (in each tablet)

Pseudoephedrine HCl 30 mg

Purpose

Nasal decongestant

Uses

- temporarily relieves sinus congestion and pressure
- temporarily relieves nasal congestion due to the common cold, hay fever or other upper respiratory allergies

Warnings

Do not use

if you are now taking a prescription monoamine oxidase inhibitor (MAOI) (certain drugs for depression, psychiatric or emotional conditions, or Parkinson’s disease), or for 2 weeks after stopping the MAOI drug. If you do not know if your prescription drug contains an MAOI, ask a doctor or pharmacist before taking this product.

Ask a doctor before use if you have

- heart disease
- high blood pressure
- thyroid disease
- diabetes
- trouble urinating due to an enlarged prostate gland

When using this product

do not exceed recommended dosage

Stop use and ask a doctor if

- nervousness, dizziness, or sleeplessness occur
- symptoms do not improve within 7 days or occur with a fever

If pregnant or breast-feeding,

ask a health professional before use.

Keep out of reach of children.

In case of overdose, get medical help or contact a Poison Control Center right away (1-800-222-1222).

Directions

adults and children 12 years and over | - take 2 tablets every 4 to 6 hours - do not take more than 8 tablets in 24 hours
children ages 6 to 11 years | - take 1 tablet every 4 to 6 hours - do not take more than 4 tablets in 24 hours
children under 6 years | do not use this product in children under 6 years of age

Other information

- each tablet contains:calcium 20 mg
- store at 20°-25°C (68°-77°F)
- do not use if blister unit is broken or torn

Inactive ingredients

carnauba wax, dibasic calcium phosphate dihydrate, FD&C red no. 40 aluminum lake, hypromellose, magnesium stearate, microcrystalline cellulose, polyethylene glycol, polysorbate 80, silicon dioxide, titanium dioxide

Questions or comments?

1-800-719-9260